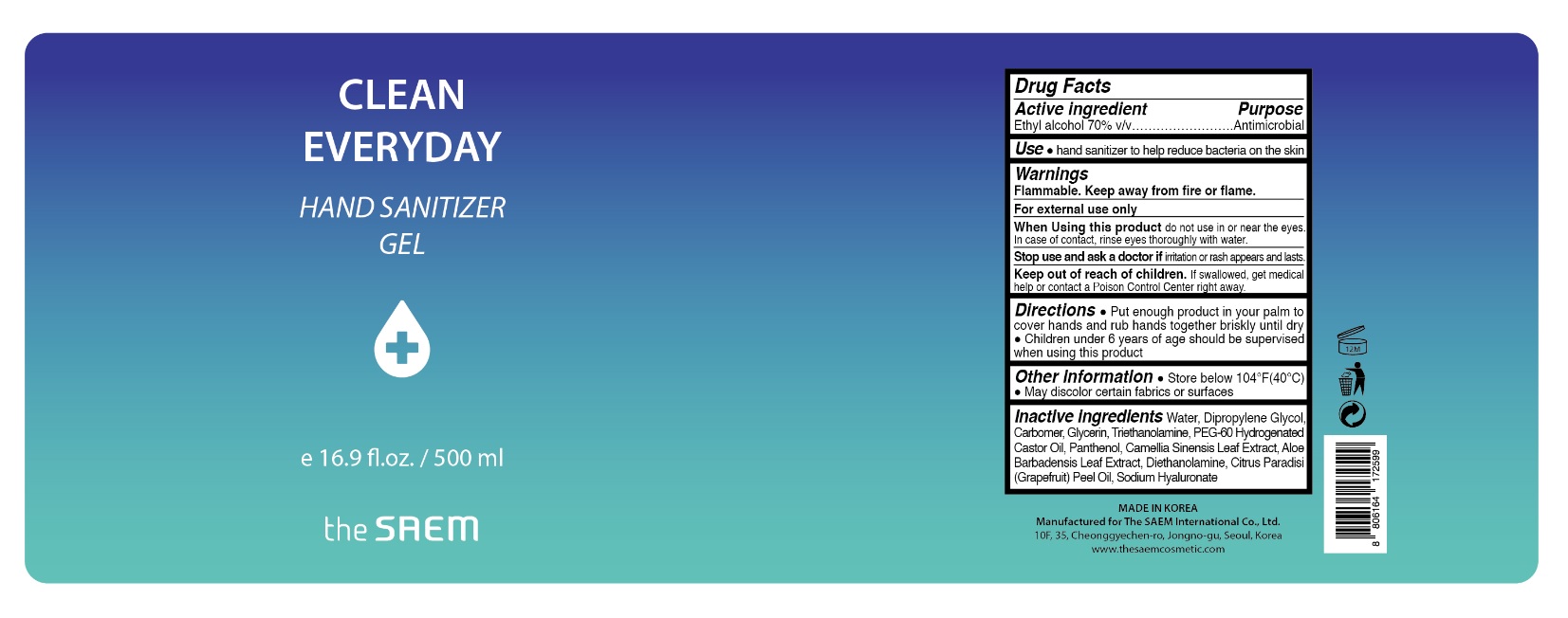 DRUG LABEL: the SAEM Clean Everyday Hand Sanitizer gel
NDC: 70341-001 | Form: GEL
Manufacturer: The Saem International Co., Ltd.
Category: otc | Type: HUMAN OTC DRUG LABEL
Date: 20200413

ACTIVE INGREDIENTS: ALCOHOL 0.7 g/1 mL
INACTIVE INGREDIENTS: WATER; DIPROPYLENE GLYCOL; CARBOMER COPOLYMER TYPE A (ALLYL PENTAERYTHRITOL CROSSLINKED); GLYCERIN; TROLAMINE; PEG-60 HYDROGENATED CASTOR OIL; PANTHENOL; GREEN TEA LEAF; ALOE VERA LEAF; DIETHANOLAMINE; GRAPEFRUIT OIL; HYALURONATE SODIUM

70341-001_the SAEM Clean Everyday Hand Sanitizer Gel

Active ingredient

Ethyl alcohol 70%

Purpose

Antimicrobial

Use

- Hand sanitizer to help reduce bacteria on the skin

Warnings

Flammable. Keep away from fire or flame.

For external use only

When using this product do not use in or near the eyes. In case of contact, rinse eyes thoroughly with water.

Stop use and ask a doctor if irritation or rash appears and lasts

Keep out of reach of children. If swallowed, get medical help or contact a Poison Control Center right away.

Directions

- Put nough produt in your palm to cover hands and rub hands together briskly until dry.
- Children under 6 years of age should be supervised when using this product

Other information

- Store below 110°F (43°C)
- May discolor certain fabrics or surfaces

Inactive ingredients

Water, Dipropylene Glycol, Carbomer, Glycerin, Triethanolamine, PEG-60 Hydrogenated Caster Oil, Panthenol, Camellia Sinensis Leaf Extract, Aloe Barbadensis Leaf Extract, Diethanolamine, Citrus Paradisi (Grapefruit) Peel Oil, Sodium Hyaluronate